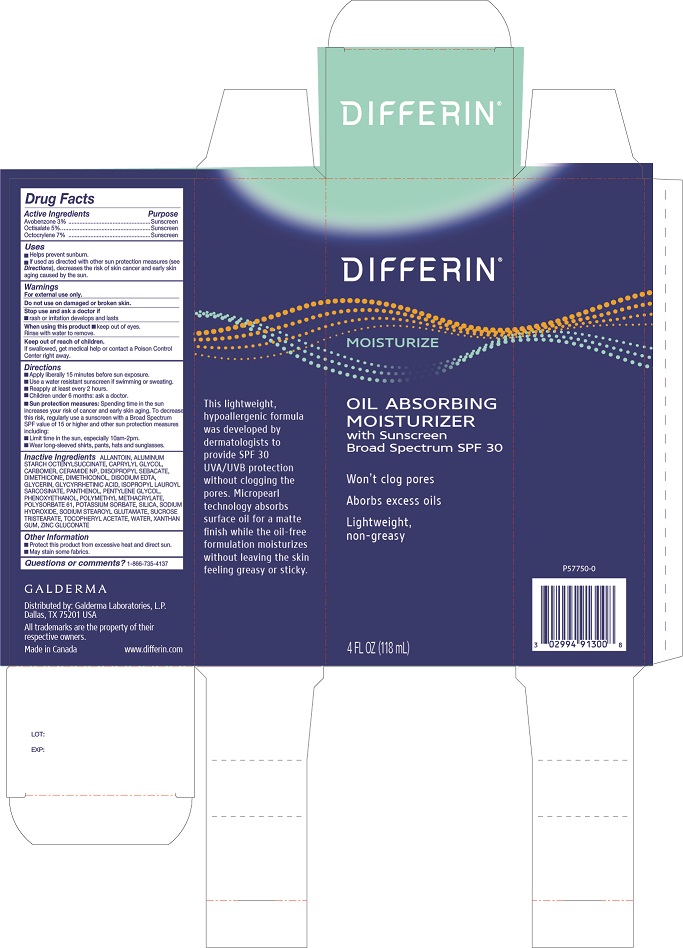 DRUG LABEL: Differin Oil Absorbing Moisturizer SPF 30
NDC: 0299-4133 | Form: LOTION
Manufacturer: Galderma Laboratories, L.P.
Category: otc | Type: HUMAN OTC DRUG LABEL
Date: 20240417

ACTIVE INGREDIENTS: Avobenzone 3 g/100 mL; Octisalate 5 g/100 mL; Octocrylene 7 g/100 mL
INACTIVE INGREDIENTS: Allantoin; Aluminum Starch Octenylsuccinate; Caprylyl Glycol; Carbomer Homopolymer Type A (Allyl Pentaerythritol Crosslinked); Ceramide Np; Diisopropyl Sebacate; Dimethicone; Dimethiconol (2000 Cst); Edetate Disodium; Glycerin; Enoxolone; Isopropyl Lauroyl Sarcosinate; Panthenol; Pentylene Glycol; Phenoxyethanol; Poly(Methyl Methacrylate; 450000 Mw); Polysorbate 61; Potassium Sorbate; Silicon Dioxide; Sodium Hydroxide; Sodium Stearoyl Glutamate; Sucrose Tristearate; .Alpha.-Tocopherol; Water; Xanthan Gum; Zinc Gluconate

Differin Oil Absorbing Moisturizer SPF 30
Galderma Laboratories, L.P.

Drug Facts

Active ingredients

AVOBENZONE 3%
OCTISALATE 5%
OCTOCRYLENE 7%

Purpose

Sunscreen

Uses

• Helps Prevent Sunburn.

• If used as directed with other sun protection measures (see Directions), decreases the risk of skin cancer and early skin aging caused by the sun.

Warnings

For external use only.

Do not use on damaged or broken skin.

Stop use and ask a doctor if
• rash or irritation develops and lasts

When using this product ∙ keep out of eyes.

Rinse with water to remove.

Keep out of reach of children.

If swallowed, get medical help or contact a Poison Control Center right away.

Directions

• Apply liberally 15 minutes before sun exposure.
• Use a water resistant sunscreen if swimming or sweating.
• Reapply at least every 2 hours.
• Children under 6 months: Ask a doctor.

• Sun protection measures: Spending time in the sun increases your risk of cancer and early skin aging. To decrease this risk, regularly use a sunscreen with a Broad Spectrum SPF value of 15 or higher and other sun protection measures including:

• Limit time in the sun, especially 10am - 2pm.

• Wear long-sleeved shirts, pants, hats, and sun glasses.

Inactive Ingredients

Allantoin, Aluminum Starch Octenylsuccinate, Caprylyl Glycol, Carbomer, Ceramide NP, Diisopropyl Sebacate, Dimethicone, Dimethiconol, Disodium EDTA, Glycerin, Glycyrrhetinic Acid, Isopropyl Lauroyl Sarcosinate, Panthenol, Pentylene Glycol, Phenoxyethanol, Polymethyl Methacrylate, Polysorbate 61, Potassium Sorbate, Silica, Sodium Hydroxide, Sodium Stearoyl Glutamate, Sucrose Tristearate, Tocopheryl Acetate, Water, Xanthan Gum, Zinc Gluconate

Other Information

- Protect this product from excessive heat and direct sun.
- May stain some fabrics.

Questions or comments?

1-866-735-4137

QUESTIONS

Distributed by:

Galderma Laboratories, L.P.
Dallas, TX 75201 USA

All trademarks at the property of their respective owners.

Made in Canada

www.differin.com

Principle Display Panel - 4 FL OZ carton

DIFFERIN®
MOISTURIZE

OIL ABSORBING
MOISTURIZER
with Sunscreen
Broad Spectrum SPF 30

Won't clog pores

Absorbs excess oils
Lightweight,
non-greasy

4 FL OZ (118 mL)
P57750-0